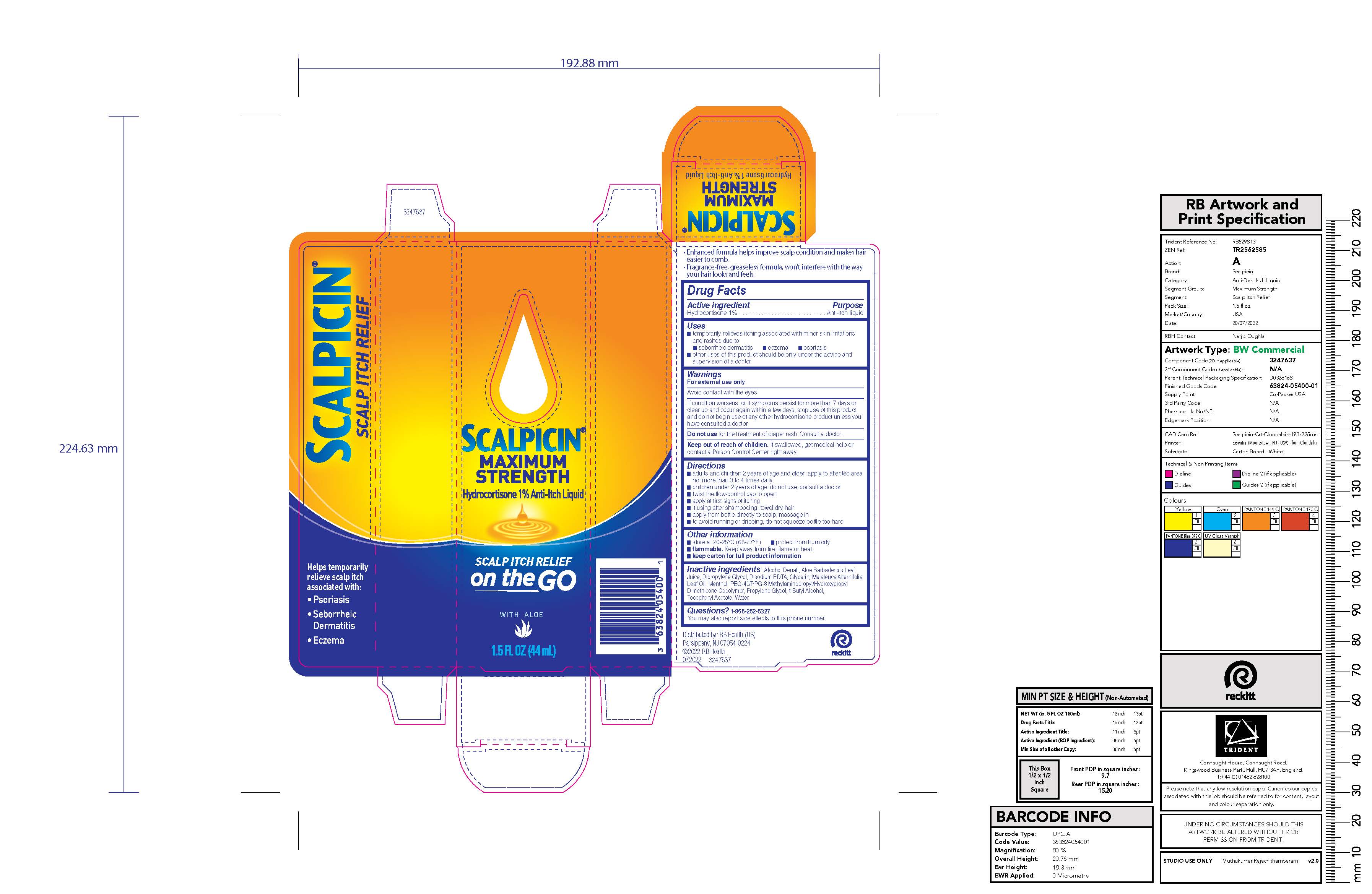 DRUG LABEL: Scalpicin
NDC: 63824-851 | Form: LIQUID
Manufacturer: RB Health (US) LLC
Category: otc | Type: HUMAN OTC DRUG LABEL
Date: 20241219

ACTIVE INGREDIENTS: HYDROCORTISONE 1 g/100 mL
INACTIVE INGREDIENTS: WATER; PROPYLENE GLYCOL; GLYCERIN; DIPROPYLENE GLYCOL; MENTHOL, UNSPECIFIED FORM; EDETATE DISODIUM; ALOE VERA LEAF; ISOPROPYL ALCOHOL; TEA TREE OIL; .ALPHA.-TOCOPHEROL ACETATE

Scalpicin®
Anti-Itch Maximum Strength

Drug Facts

Active ingredient

Hydrocortisone 1%

Purpose

Anti-itch liquid

Uses

- temporarily relieves itching associated with minor skin irritations and rashes due to
  - seborrheic dermatitis
  - eczema
  - psoriasis
- other uses of this product should be only under the advice and supervision of a doctor

Warnings

For external use only

Avoid contact with the eyes

If condition worsens, or if symptoms persist for more than 7 days or clear up and occur again within a few days, stop use of this product and do not begin use of any other hydrocortisone product unless you have consulted a doctor

Do not use for the treatment of diaper rash. Consult a doctor.

Keep out of reach of children. If swallowed, get medical help or contact a Poison Control Center right away.

Directions

- adults and children 2 years of age and older: apply to affected area not more than 3 to 4 times daily
- children under 2 years of age: do not use; consult a doctor
- twist the flow-control cap to open
- apply at first signs of itching
- if using after shampooing, towel dry hair
- apply from bottle directly to scalp, massage in
- to avoid running or dripping, do not squeeze bottle too hard

Other information

- store at 20-25 °C (68-77°F)
- protect from humidity
- flammable. Keep away from fire, flame or heat.
- keep carton for full product information

Inactive ingredients

Alcohol Denat., Aloe Barbadensis Leaf Juice, Dipropylene Glycol, Disodium EDTA, Glycerin, Melaleuca Alternifolia Leaf Oil, Menthol, PEG-40/PPG-8 Methylaminopropyl/Hydroxypropyl Dimethicone Copolymer, Propylene Glycol, t-Butyl Alcohol, Tocopheryl Acetate, Water

Questions?

1-866-252-5327

You may also report side effects to this phone number.

Distributed by: RB Health (US)
Parsippany, NJ 07054-0224

PRINCIPAL DISPLAY PANEL - 44 mL Bottle Carton

SCALPICIN®
MAXIMUM
STRENGTH

Hydrocortisone 1% Anti-Itch Liquid

SCALP ITCH RELIEF
on the GO

WITH ALOE

1.5 FL OZ (44 mL)